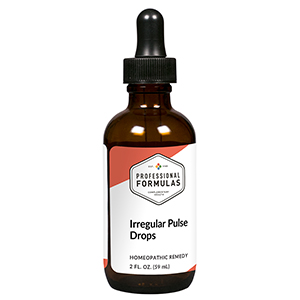 DRUG LABEL: Irregular Pulse Drops
NDC: 63083-2036 | Form: LIQUID
Manufacturer: Professional Complementary Health Formulas
Category: homeopathic | Type: HUMAN OTC DRUG LABEL
Date: 20190815

ACTIVE INGREDIENTS: HAWTHORN LEAF WITH FLOWER 1 [hp_X]/59 mL; VALERIAN 1 [hp_X]/59 mL; VISNAGA DAUCOIDES FRUIT 2 [hp_X]/59 mL; POTASSIUM PHOSPHATE, UNSPECIFIED FORM 2 [hp_X]/59 mL; LEONURUS CARDIACA WHOLE 2 [hp_X]/59 mL; CYTISUS SCOPARIUS FLOWERING TOP 3 [hp_X]/59 mL; SPIGELIA ANTHELMIA WHOLE 3 [hp_X]/59 mL; NERIUM OLEANDER WHOLE 4 [hp_X]/59 mL; CINCHONA OFFICINALIS BARK 6 [hp_X]/59 mL; DIGITALIS 6 [hp_X]/59 mL; BEEF HEART 6 [hp_X]/59 mL; IBERIS AMARA SEED 6 [hp_X]/59 mL; POTASSIUM CARBONATE 6 [hp_X]/59 mL; FERULA SUMBUL ROOT 6 [hp_X]/59 mL
INACTIVE INGREDIENTS: ALCOHOL; WATER

C36

ACTIVE INGREDIENTS

Crataegus oxyacantha 1X
Valeriana officinalis 1X
Ammi visnaga 2X
Kali phosphoricum 2X
Leonurus cardiaca 2X
Cytisus scoparius 3X
Spigelia anthelmia 3X
Oleander 4X
Cinchona officinalis 6X
Digitalis purpurea 6X
Heart 6X
Iberis amara 6X
Kali carbonicum 6X
Sumbul 6X

QUESTIONS

Professional Formulas

PO Box 2034 Lake Oswego, OR 97035

INDICATIONS

For the temporary relief of a minor change in heartbeat due to stress, pain in other areas of the body, smoking, drinking alcohol or caffeine, or taking stimulants.*

PURPOSE

*Claims based on traditional homeopathic practice, not accepted medical evidence. Not FDA evaluated.

WARNINGS

An irregular heartbeat may be a sign of a serious condition. Consult a doctor promptly if symptoms persist or are accompanied by fluttering in the chest, chest pain, fainting, or dizziness. Keep out of the reach of children. In case of overdose, get medical help or contact a poison control center right away. If pregnant or breastfeeding, ask a healthcare professional before use.

Keep out of the reach of children.

PREGNANCY OR BREAST FEEDING

If pregnant or breastfeeding, ask a healthcare professional before use.

DIRECTIONS

Place drops under tongue 30 minutes before/after meals. Adults and children 12 years and over: Take 10 drops up to 3 times per day. Consult a physician for use in children under 12 years of age.

OTHER INFORMATION

Tamper resistant. If seal is broken, do not use. After opening, close container tightly and store at room temperature away from heat.

INACTIVE INGREDIENTS

20% ethanol, purified water.

LABEL

Est 1985

Professional Formulas

Complementary Health

Irregular Pulse Drops

Homeopathic Remedy

2 FL. OZ. (59 mL)